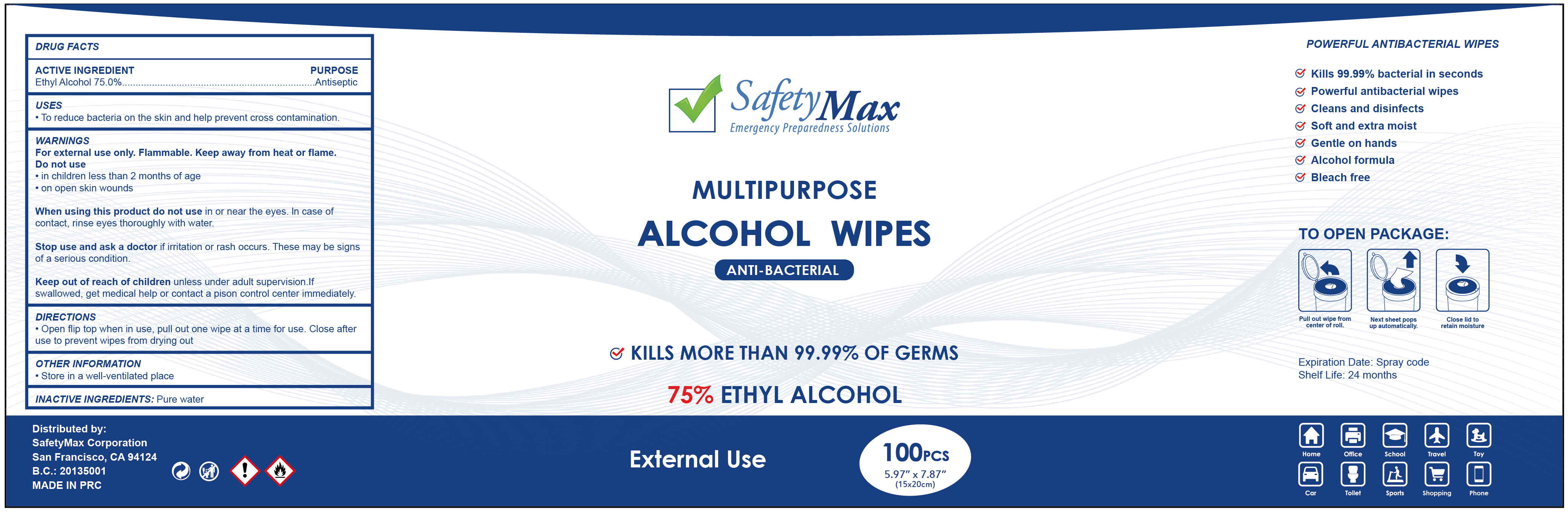 DRUG LABEL: SafetyMax Alcohol wipes
NDC: 78183-010 | Form: CLOTH
Manufacturer: Kunming Ansheng Industry & Trade Co., Ltd.
Category: otc | Type: HUMAN OTC DRUG LABEL
Date: 20200903

ACTIVE INGREDIENTS: ALCOHOL 0.75 U/1 U
INACTIVE INGREDIENTS: WATER

SafetyMax 75% ALCOHOL WIPES

Active Ingredient(s)

Alcohol 75.0% v/v.

Purpose

To reduce bacteria on the skin and help prevent cross contamination.

Use

Hand sanitizer to help reduce bacteria on the skin.

Warnings

For external use only. Flammable. Keep away from heat or flame

Do not use

- on children less than 2 months of age.
- on open skin wounds

When using this product do not use in or contact the eyes or damaged skin. In case of contact, rinse eyes thoroughly with water.

Stop use and ask a doctor if irritation or rash appears and lasts. These may be signs of a serious condition.

Keep out of reach of children unless under adult supervision. If swallowed, get medical help or contact a Poison Control Center right away.

Directions

- Open flip top when in use, pull out one wipe at a time for use.
- Close after use to prevent wipes from drying out.

Inactive ingredients

Pure water.

OTHER INFORMATION

• Store in a well-ventilated place.

Package Label - Principal Display Panel

100 wipes in 1 canister.

NDC: 78183-010-01;